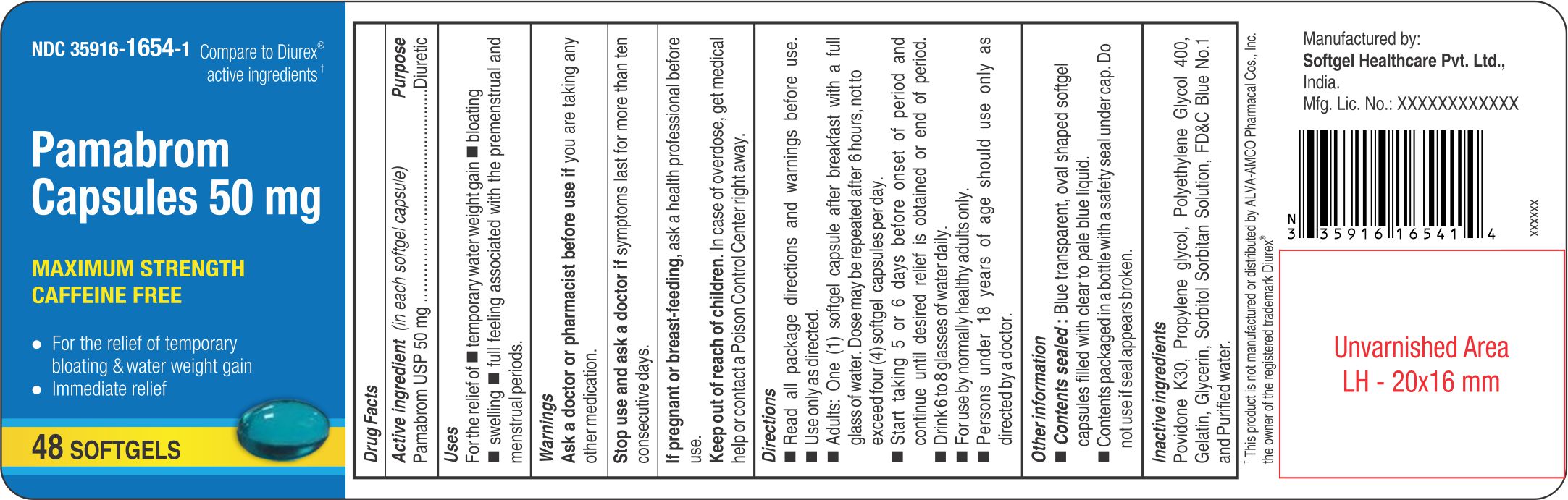 DRUG LABEL: Pamabrom
NDC: 35916-1654 | Form: CAPSULE, LIQUID FILLED
Manufacturer: Softgel Healthcare Pvt Ltd
Category: otc | Type: HUMAN OTC DRUG LABEL
Date: 20260127

ACTIVE INGREDIENTS: PAMABROM 50 mg/1 1
INACTIVE INGREDIENTS: GELATIN; GLYCERIN; SORBITOL; WATER; FD&C BLUE NO. 1; POVIDONE K30; POLYETHYLENE GLYCOL 400; PROPYLENE GLYCOL

Pamabrom Capsules 50 mg

Active ingredient (in each softgel capsule)

Pamabrom USP 50 mg

Purpose

Diuretic

Uses

For the relief of

temporary water weight gain
bloating
swelling
full feeling associated with the premenstrual and menstrual periods.

Ask a doctor or pharmacist before use if

you are taking any other medication.

Stop use and ask a doctor if

symptoms last for more than ten consecutive days.

If pregnant or breast-feeding

ask a health professional before use.

Keep out of reach of chlidren

In case of overdose, get medical help or contact a Poison Control Center right away.

Directions

- Read all package directions and warnings before use.
- Use only as directed.
- Adults: One (1) softgel capsule after breakfast with a full glass of water, Dose may be repeated after 6 hours, not to exceed four (4) softgel capsules per day.
- Start taking 5 or 6 days before onset of period and continue until desired relief is obtained or end of period.
- Drink 6 to 8 glasses of water daily.
- For use by normally healthy adults only.
- Persons under 18 years of age should use only as directed by a doctor.

Other information

- Contents sealed: Blue transparent, oval shaped softgel capsules filled with clear to pale blue liquid.
- Contents packaged in a bottle with a safety seal under cap. Do not use if seal appears broken.

Inactive ingredients

Povidone K30, Propylene glycol, Polyethylene Glycol 400, Gelatin, Glycerin, Sorbitol Sorbitan Solution, FD&C Blue No.1 and Purified water.